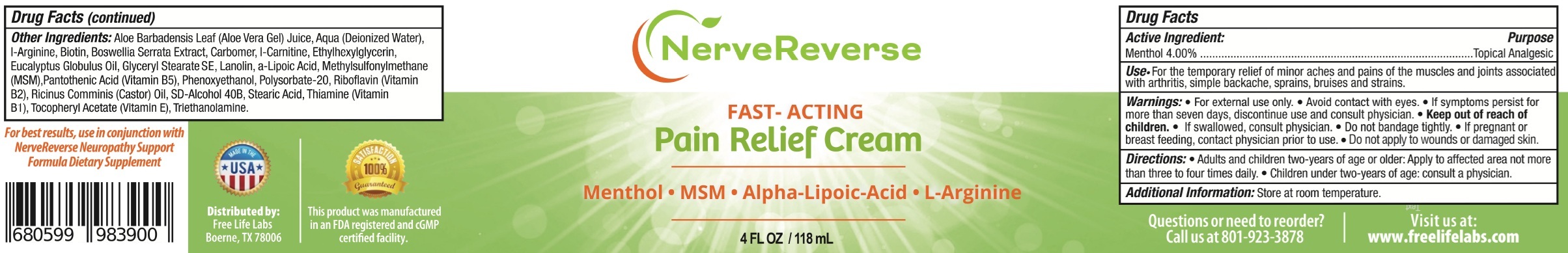 DRUG LABEL: NERVE REVERSE PAIN RELIEF
NDC: 73067-870 | Form: CREAM
Manufacturer: Pogue Medical Services
Category: otc | Type: HUMAN OTC DRUG LABEL
Date: 20250623

ACTIVE INGREDIENTS: MENTHOL 40 mg/1 mL
INACTIVE INGREDIENTS: ALOE VERA LEAF; WATER; ARGININE; BIOTIN; INDIAN FRANKINCENSE; CARBOXYPOLYMETHYLENE; LEVOCARNITINE; ETHYLHEXYLGLYCERIN; EUCALYPTUS OIL; GLYCERYL MONOSTEARATE; LANOLIN; DIMETHYL SULFONE; PANTOTHENIC ACID; PHENOXYETHANOL; POLYSORBATE 20; RIBOFLAVIN; STEARIC ACID; .ALPHA.-TOCOPHEROL ACETATE; TROLAMINE

NERVE REVERSE PAIN RELIEF CREAM

Active Ingredient:

Menthol 4.00%

Purpose

Topical Analgesic

Use

- For the temporary relief of minor aches and pains of the muscles and joints associated with arthritis, simple backache, sprains, bruises and strains.

Warnings:

- For external use only.
- Avoid contact with eyes.
- If symptoms persist for more than seven days, discontinue use and consult physician.

Keep out of reach of children.

- If swallowed, consult physician.
- Do not bandage tightly.

If pregnant or breast feeding,

contact physician prior to use.

Directions

Adults and children two-years of age or older: Apply to affected area not more than three to four times daily.

- Children under two-years of age: consult a physician.

Additional Information:

Store at room temperature.

Other Ingredients:

Aloe Barbadensis Leaf (Aloe Vera Gel) Juice, Aqua (Deionized Water), l-Arginine, Biotin, Boswellia Serrata Extract, Carbomer, l-Carnitine, Ethylhexylglycerin, Eucalyptus Globulus Oil, Glyceryl Stearate, Lanolin, a-Lipoic Acid, Methylsulfonylmethane (MSM), Pantothenic Acid (Vitamin B5), Phenoxyethanol, Polysorbate-20, Riboflavin (Vitamin B2), Ricinus Comminis (Castor) Oil, SD-Alcohol 40B, Stearic Acid, Thiamine (Vitamin B1), Tocopheryl Acetate (Vitamin E), Triethanolamine.